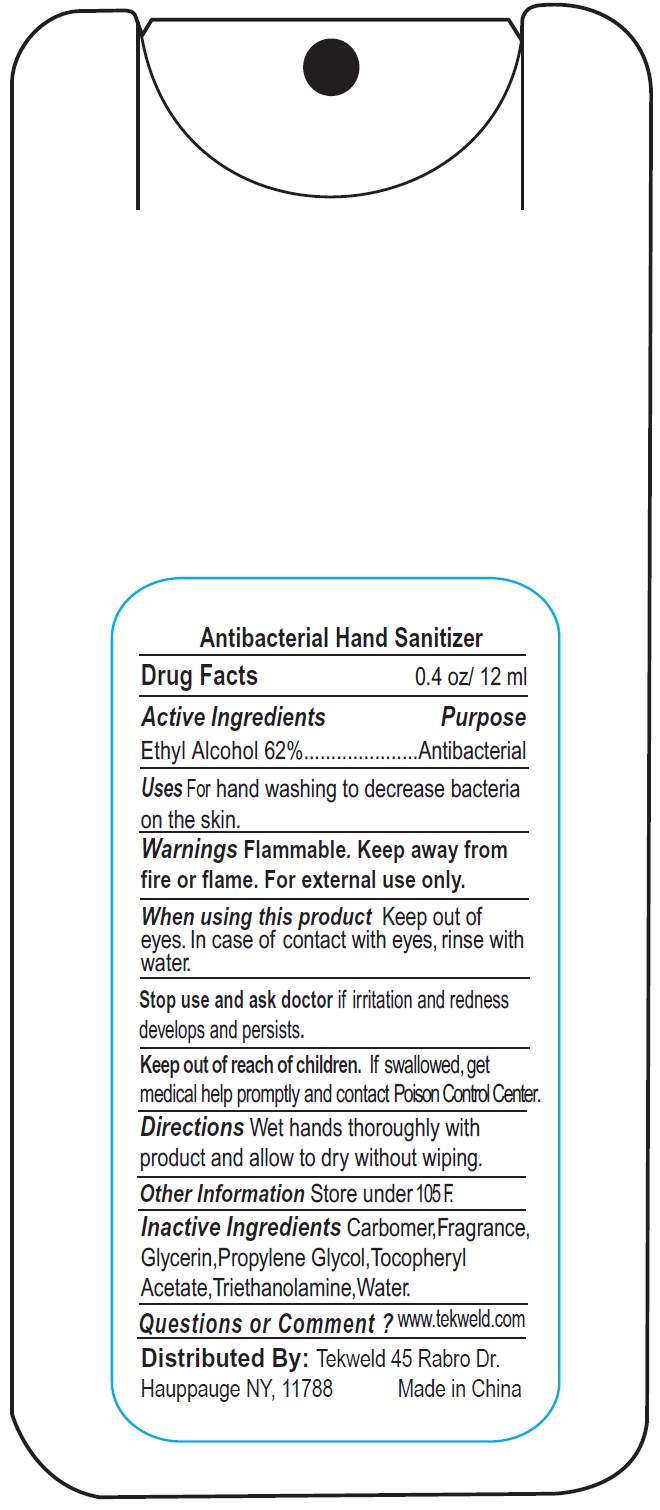 DRUG LABEL: Antibacterial Hand Sanitizer
NDC: 71160-188 | Form: LIQUID
Manufacturer: TEKWELD INC
Category: otc | Type: HUMAN OTC DRUG LABEL
Date: 20240112

ACTIVE INGREDIENTS: ALCOHOL 62 mL/100 mL
INACTIVE INGREDIENTS: CARBOMER HOMOPOLYMER, UNSPECIFIED TYPE; GLYCERIN; PROPYLENE GLYCOL; .ALPHA.-TOCOPHEROL ACETATE; TROLAMINE; WATER

Antibacterial Hand Sanitizer

Active Ingredients

Ethyl Alcohol 62%

Purpose

Antibacterial

Uses

For hand washing to decrease bacteria on the skin.

Warnings

Flammable. Keep away from fire or flame. For external use only.

When using this product

Keep out of eyes. In case of contact with eyes, rinse with water.

Stop use and ask doctor

if irritation and redness develops and persists.

Keep out of reach of children.

If swallowed, get medical help promptly and contact Poison Control Center

Directions

Wet hands thoroughly with product and allow to dry without wiping.

Other information

Store under 105°f.

Inactive Ingredients

Carbomer,Fragrance, Glycerin,Propylene Glycol,Tocopheryl Acetate,Triethanolamine,Water.

Questions or Comment ?

www.tekweld.com